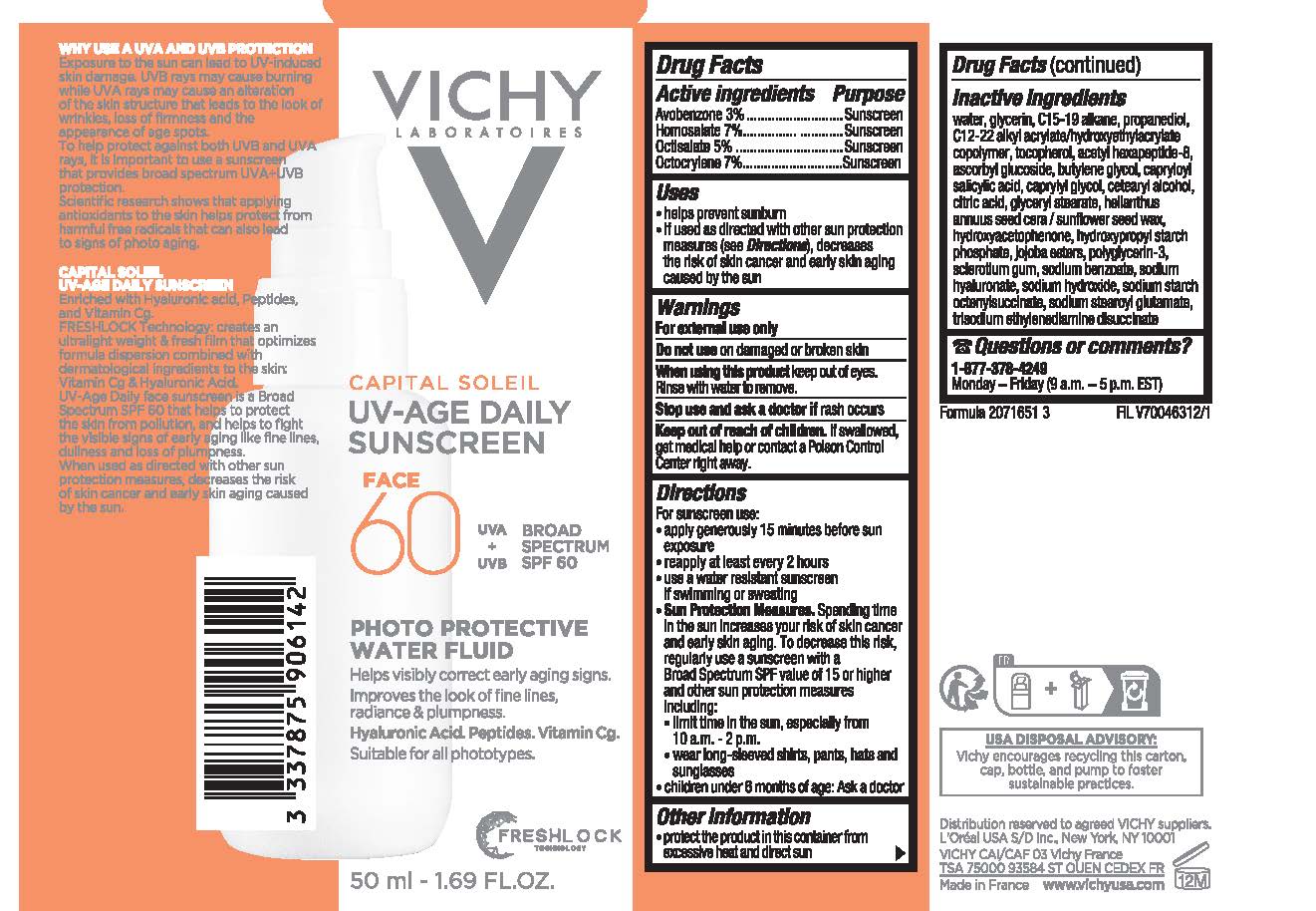 DRUG LABEL: Vichy Laboratoires Capital Soleil UV Age Daily Sunscreen Broad Spectrum SPF 60
NDC: 49967-995 | Form: LOTION
Manufacturer: L’Oreal USA Products Inc
Category: otc | Type: HUMAN OTC DRUG LABEL
Date: 20240714

ACTIVE INGREDIENTS: AVOBENZONE 30 mg/1 mL; homosalate 70 mg/1 mL; octisalate 50 mg/1 mL; octocrylene 70 mg/1 mL
INACTIVE INGREDIENTS: WATER; GLYCERIN; C15-19 ALKANE; PROPANEDIOL; TOCOPHEROL; ACETYL HEXAPEPTIDE-8; ASCORBYL GLUCOSIDE; BUTYLENE GLYCOL; CAPRYLOYL SALICYLIC ACID; CAPRYLYL GLYCOL; CETOSTEARYL ALCOHOL; CITRIC ACID MONOHYDRATE; GLYCERYL 1-STEARATE; HELIANTHUS ANNUUS SEED WAX; HYDROXYACETOPHENONE; POLYGLYCERIN-3; BETASIZOFIRAN; SODIUM BENZOATE; HYALURONATE SODIUM; SODIUM HYDROXIDE; SODIUM STEAROYL GLUTAMATE; TRISODIUM ETHYLENEDIAMINE DISUCCINATE

Drug Facts

Active ingredients

Avobenzone 3%

Homosalate 7%

Octisalate 5%

Octocrylene 7%

Purpose

Sunscreen

Uses

- helps prevent sunburn
- if used as directed with other sun protection measures (see Directions), decreases the risk of skin cancer and early skin aging caused by the sun

Warnings

For external use only

Do not use

on damaged or broken skin

When using this product

keep out of eyes. Rinse with water to remove.

Stop use and ask a doctor if

rash occurs

Keep out of reach of children.

If swallowed, get medical help or contact a Poison Control Center right away.

Directions

For sunscreen use:

- shake well before use

● apply liberally 15 minutes before sun exposure

● reapply:

● after 80 minutes of swimming or sweating

● immediately after towel drying

● at least every 2 hours

● Sun Protection Measures. Spending time in the sun increases your risk of skin cancer and early skin aging. To decrease this risk, regularly use a sunscreen with a Broad Spectrum SPF value of 15 or higher and other sun protection measures including:

● limit time in the sun, especially from 10 a.m. – 2 p.m.

● wear long-sleeved shirts, pants, hats, and sunglasses

● children under 6 months of age: Ask a doctor

Other information

- protect the product in this container from excessive heat and direct sun
- store at 68 – 77° F (20 – 25°C)

Inactive ingredients

water, glycerin, c15-19 alkane, propanediol, C12-22 alkyl acrylate/hydroxyethylacrylate copolymer, tocopherol, acetyl hexapeptide-8, ascorbyl glucoside, butylene glycol, capryloyl salicylic acid, caprylyl glycol, cetearyl alcohol, citric acid, glyceryl stearate, helianthus annuus (sunflower) seed wax, hydroxyacetophenone, hydroxypropyl starch phosphate, jojoba esters, polyglycerin-3, sclerotium gum, sodium benzoate, sodium hyaluronate, sodium hydroxide, sodium starch octenylsuccinate, sodium stearoyl glutamate, trisodium ethylenediamine disuccinate

Questions or comments?

Call toll free 1-877-378-4249

Monday - Friday (9 a.m. to 5 p.m. EST)